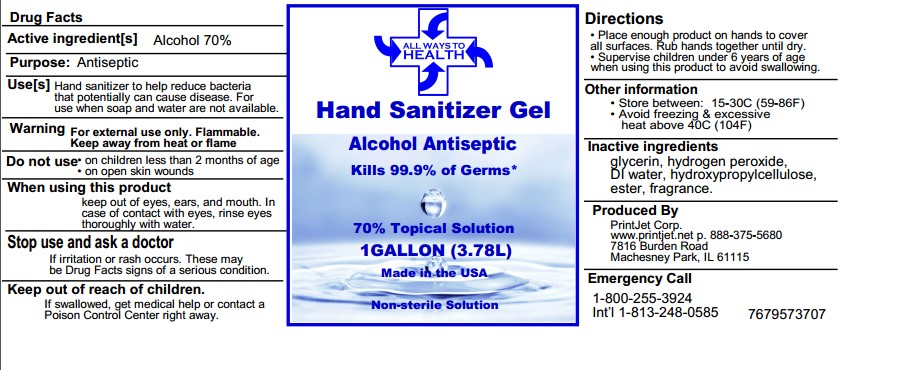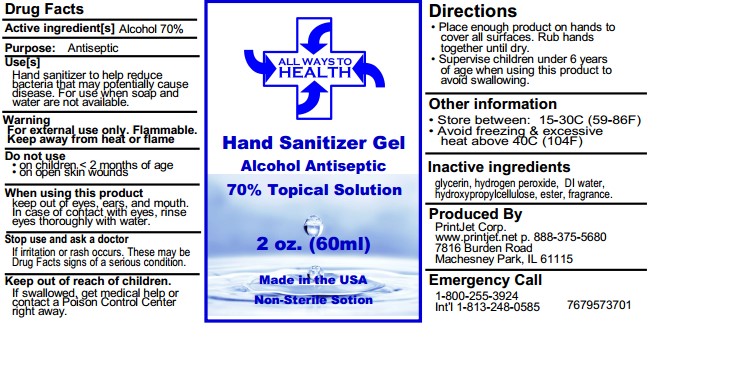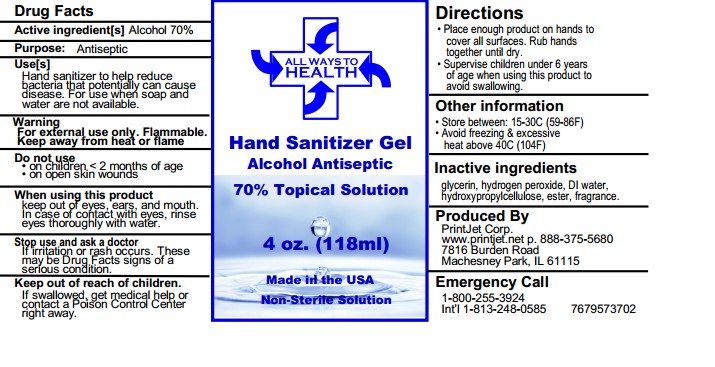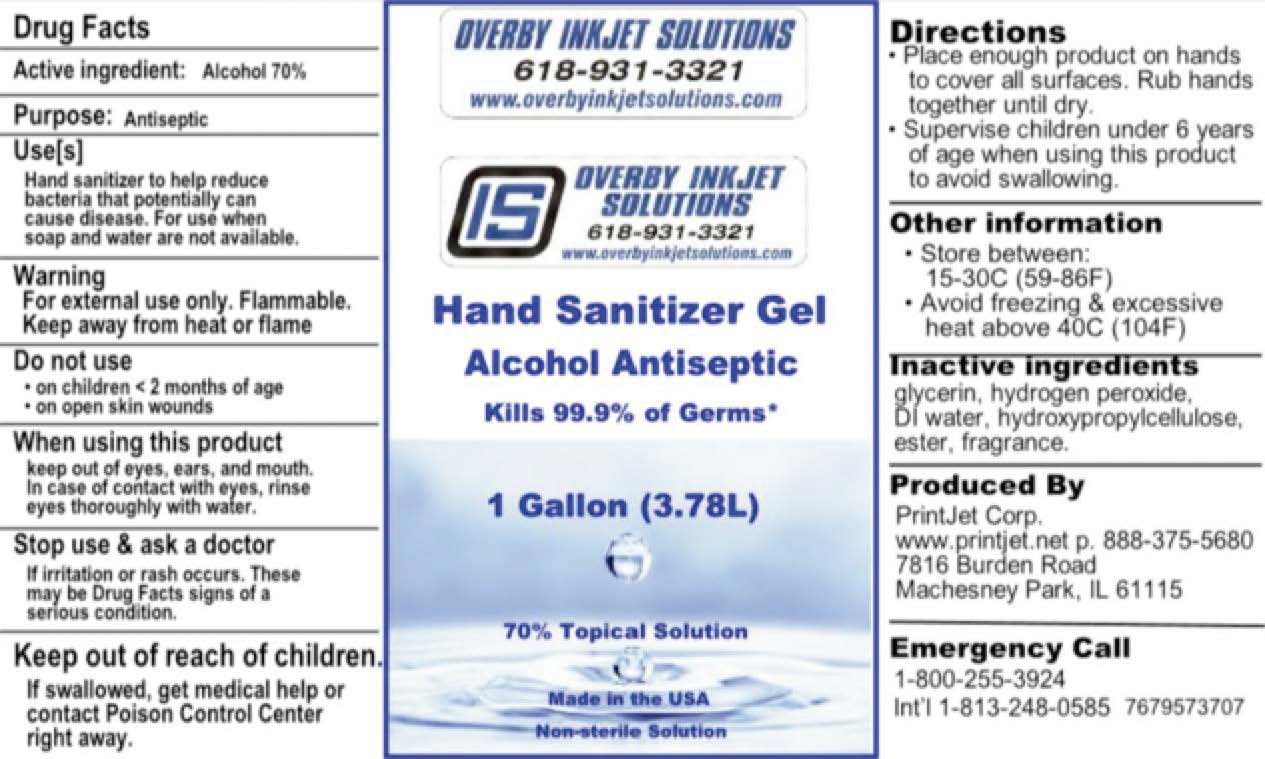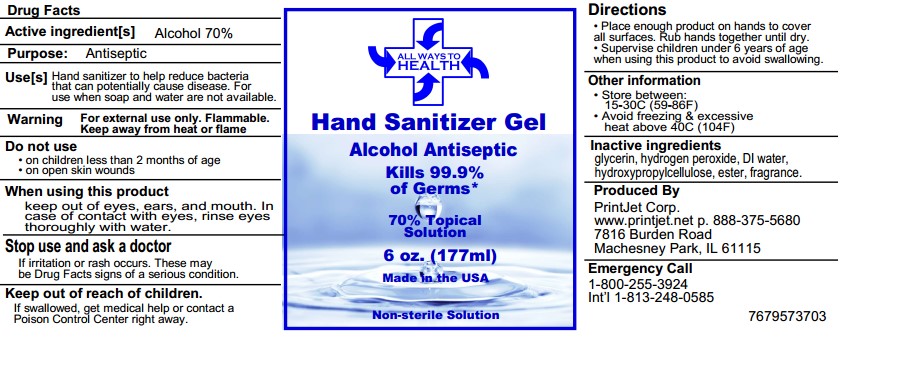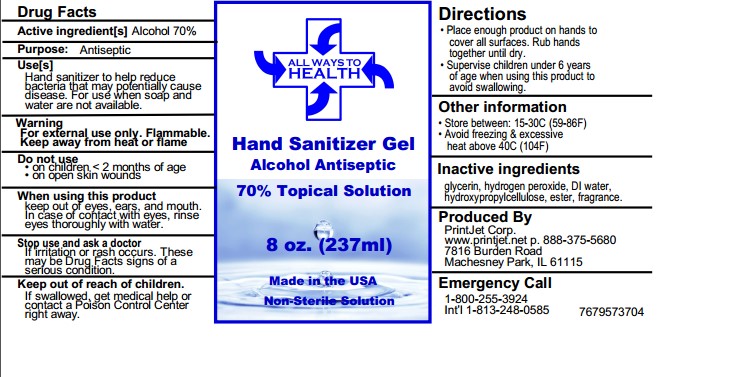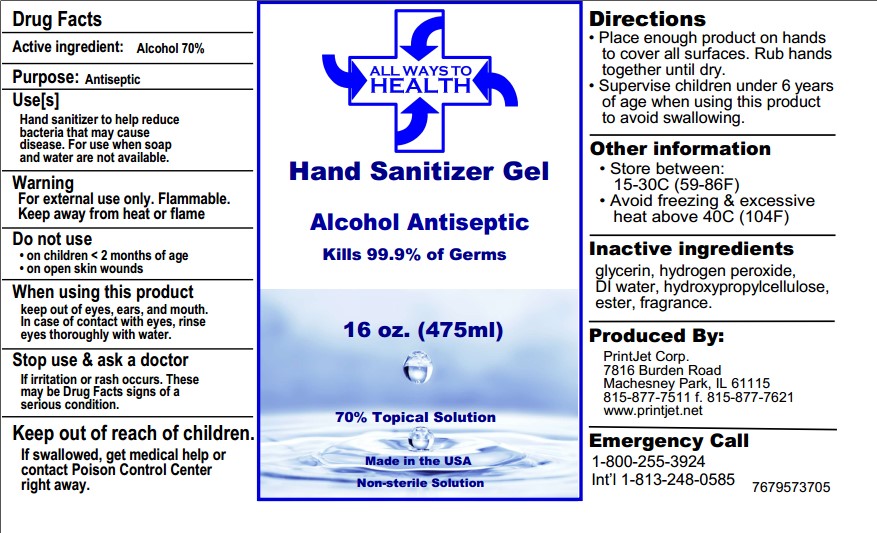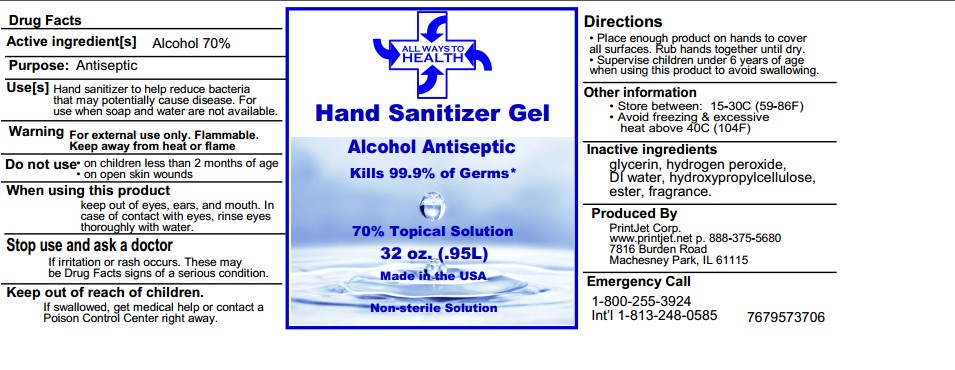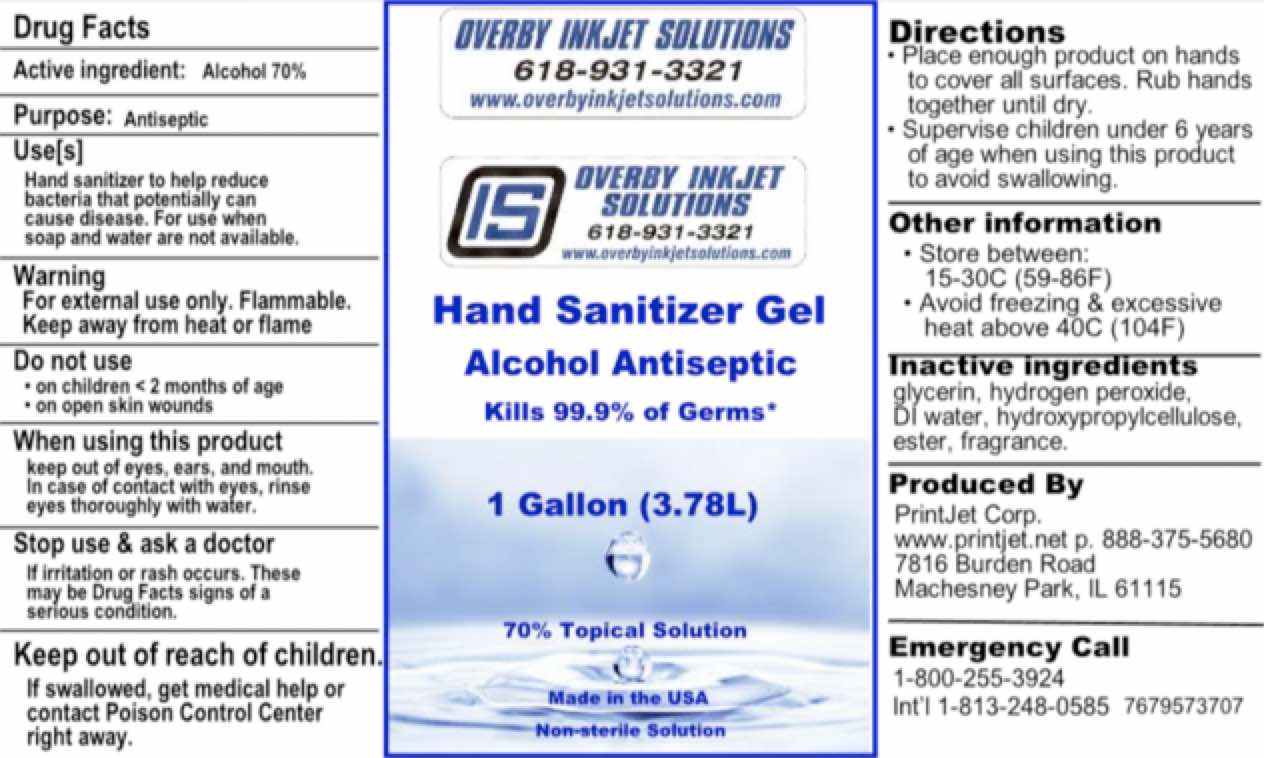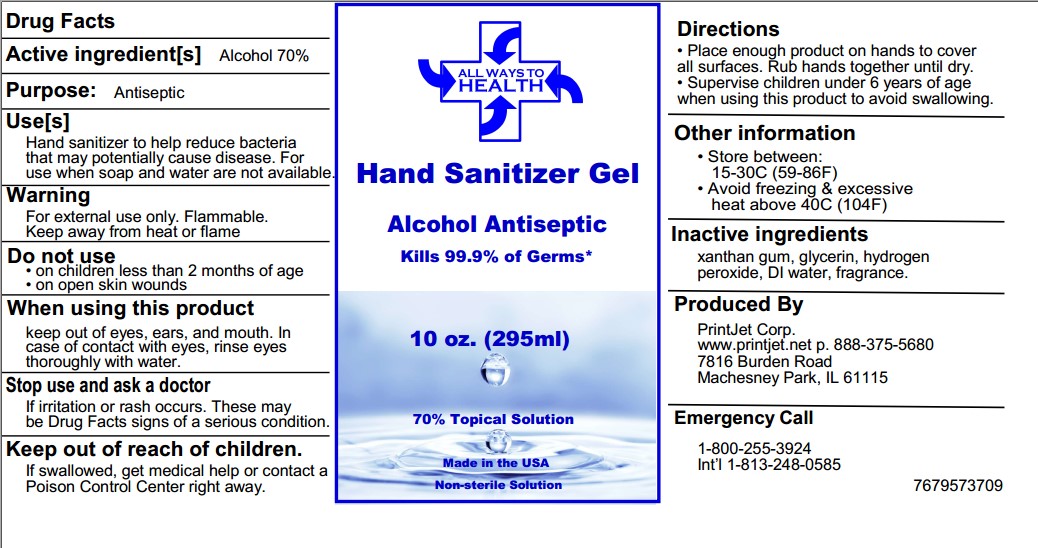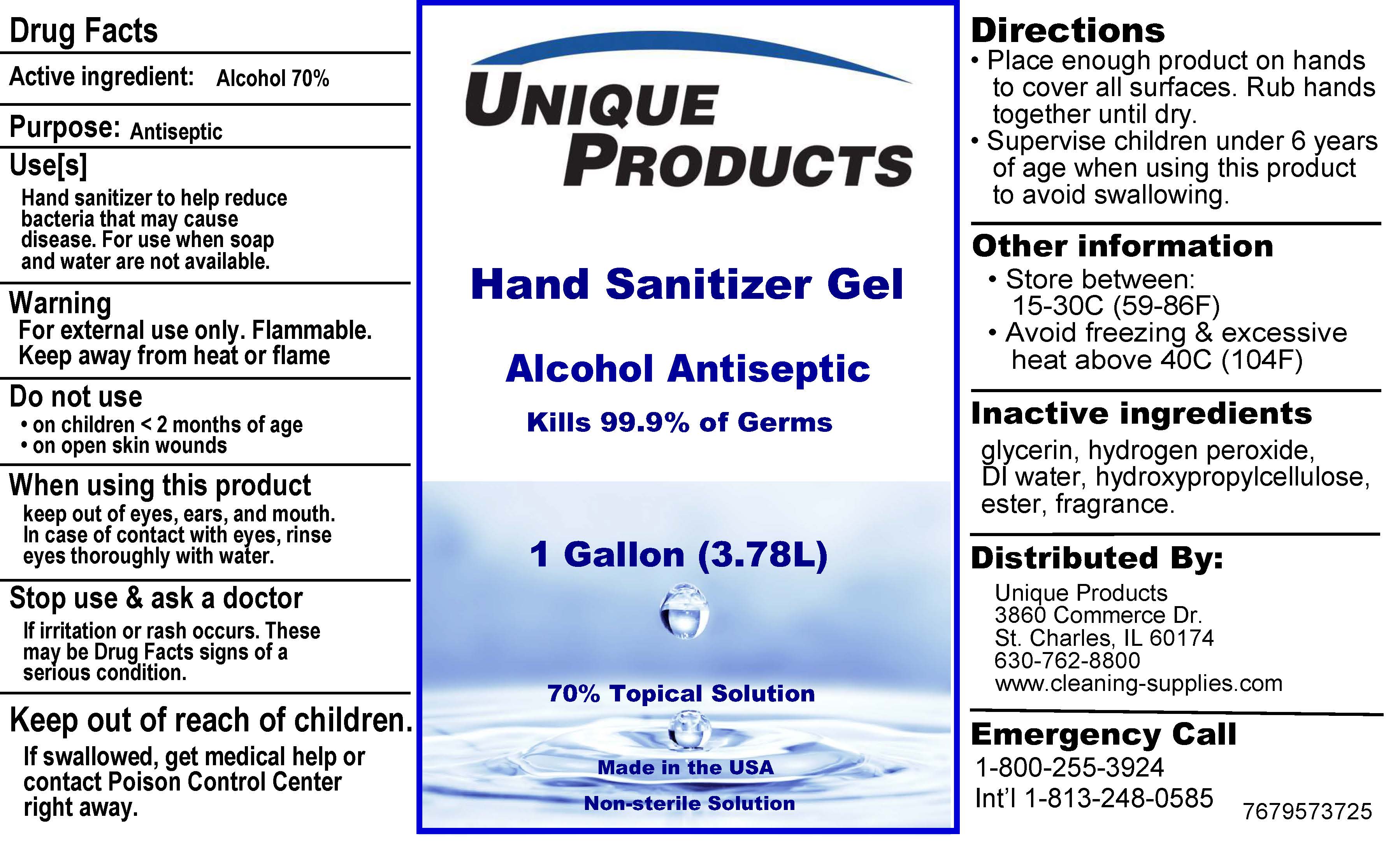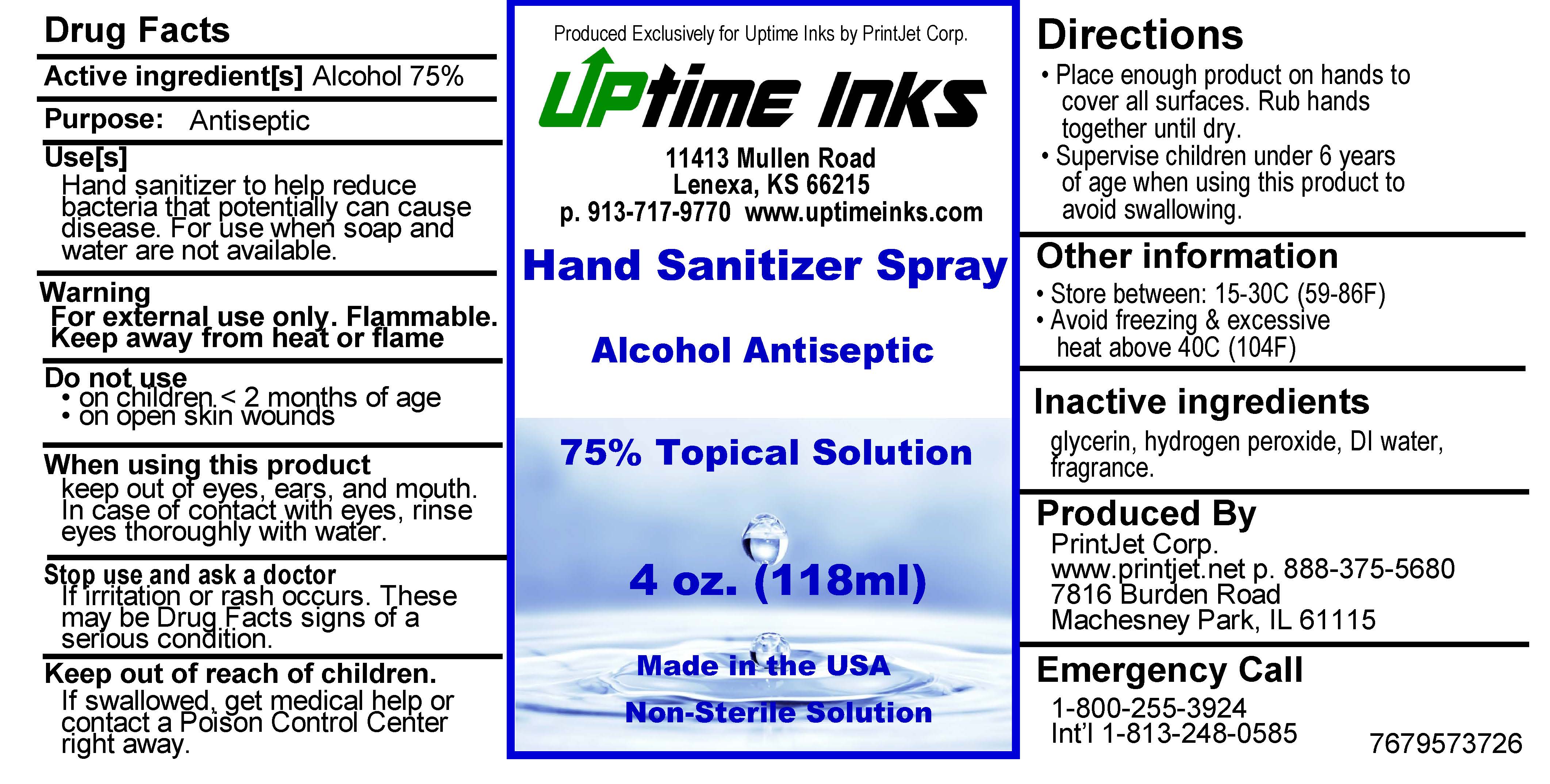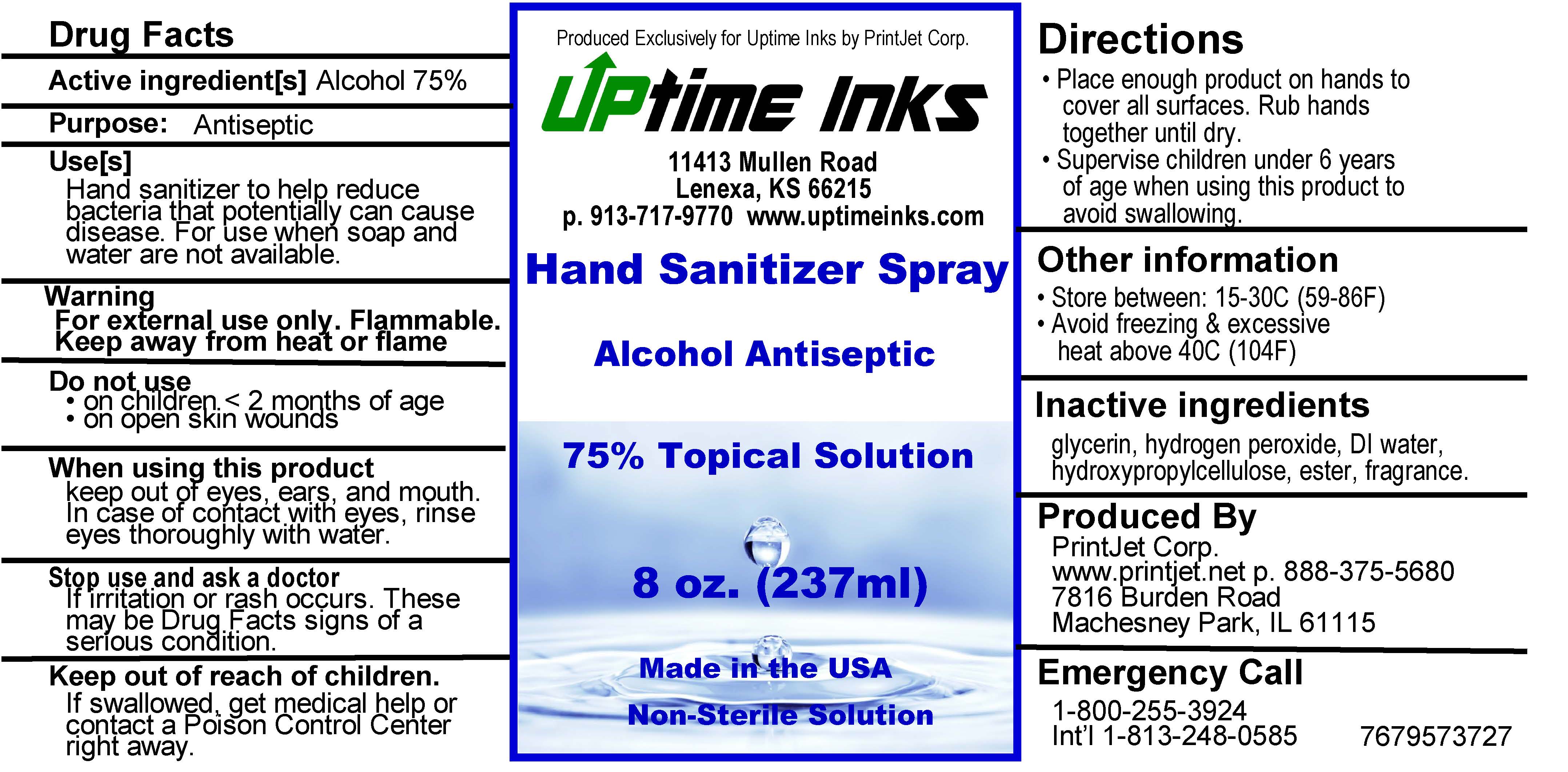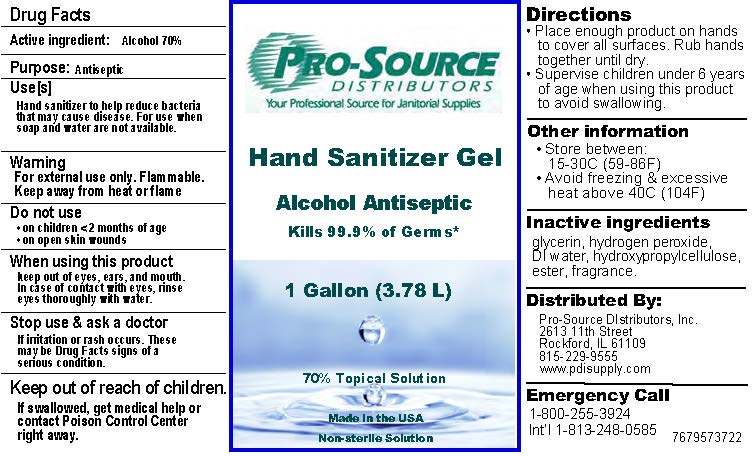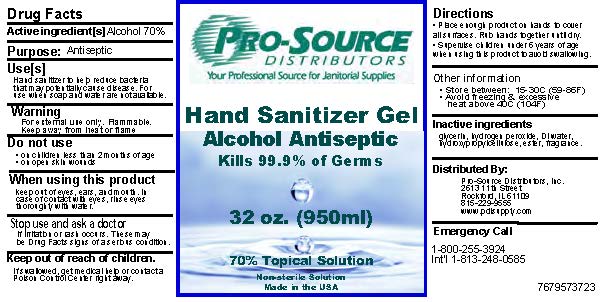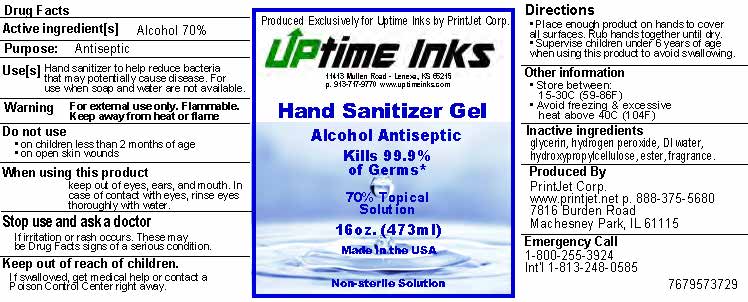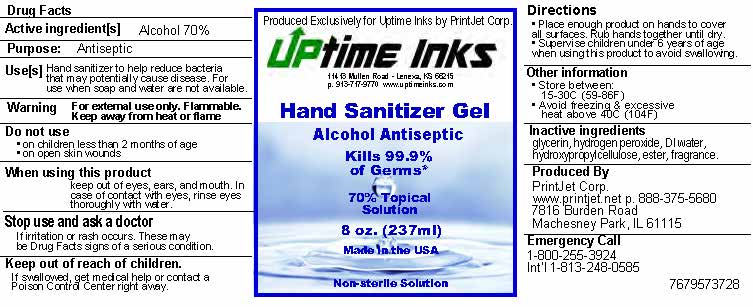 DRUG LABEL: Hand Sanitizer
NDC: 76795-737 | Form: GEL
Manufacturer: PrintJet Corp
Category: otc | Type: HUMAN OTC DRUG LABEL
Date: 20201006

ACTIVE INGREDIENTS: ALCOHOL 75.225 mL/100 mL
INACTIVE INGREDIENTS: (2-(((2-(2-AMINO-3-HYDROXY-2-(HYDROXYMETHYL)PROPOXY)-1-HYDROXYPROPYL)HYDROXYPHOSPHORYL)OXY)-1-HYDROXYPROPYL)PHOSPHONIC ACID 1.1 mL/100 mL; GLYCERIN 1.3 mL/100 mL; HYDROGEN PEROXIDE 0.125 mL/100 mL; WATER 22.225 mL/100 mL; FRAGRANCE LAVENDER & CHIA F-153480 0.025 mL/100 mL

Active Ingredient(s)

Alcohol 70% v/v. Purpose: Antiseptic

Purpose

Antiseptic, Hand Sanitizer

Use

Hand Sanitizer to help reduce bacteria that potentially can cause disease. For use when soap and water are not available.

Warnings

For external use only. Flammable. Keep away from heat or flame

Do not use

- in children less than 2 months of age
- on open skin wounds

When using this product keep out of eyes, ears, and mouth. In case of contact with eyes, rinse eyes thoroughly with water.
Stop use and ask a doctor if irritation or rash occurs. These may be signs of a serious condition.
Keep out of reach of children. If swallowed, get medical help or contact a Poison Control Center right away.

Stop use and ask a doctor if irritation or rash occurs. These may be signs of a serious condition.

Keep out of reach of children. If swallowed, get medical help or contact a Poison Control Center right away.

Directions

- Place enough product on hands to cover all surfaces. Rub hands together until dry.
- Supervise children under 6 years of age when using this product to avoid swallowing.

Other information

- Store between 15-30C (59-86F)
- Avoid freezing and excessive heat above 40C (104F)

Inactive ingredients

glycerin, hydrogen peroxide, purified water USP, fragrance, Hydroxypropylcellulose

Package Label - Principal Display Panel

118 ML NDC: 76795-737-26

3785 ML NDC: 76795-737-25

473 ML NDC: 76795-737-29

236 ML NDC: 76795-737-28

236 ML NDC: 76795-737-27

118 ML NDC: 76795-737-26

3758 ML NDC: 76795-737-25

60 ML NDC: 76795-737-01

118 ML NDC: 76795-737-02

177 ML NDC: 76795-737-03

237 ML NDC: 76795-737-04

296 ML NDC: 76795-737-09

473 ML NDC: 76795-737-05

946 ML NDC: 76795-737-06

3785 ML NDC: 76795-737-07

3785 ML NDC: 76795-737-22

946 ML NDC: 76795-737-23